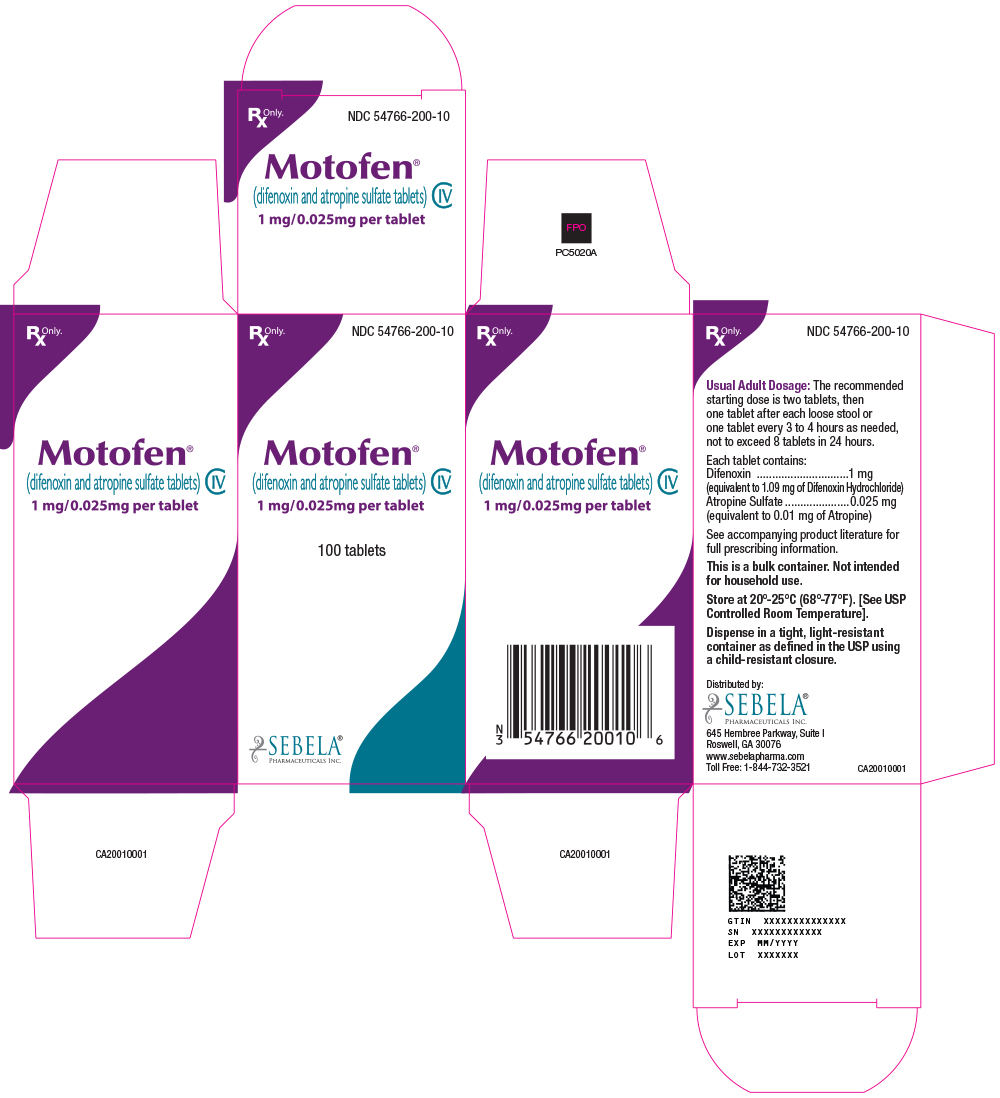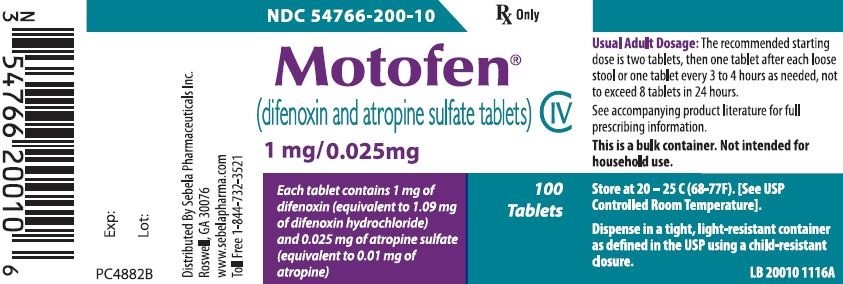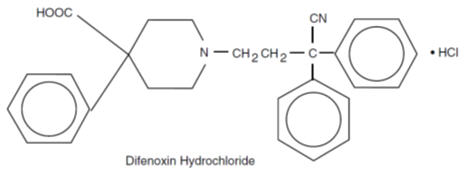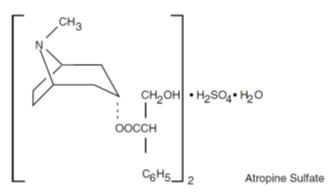 DRUG LABEL: Motofen
NDC: 54766-200 | Form: TABLET
Manufacturer: Sebela Pharmaceuticals Inc.
Category: prescription | Type: HUMAN PRESCRIPTION DRUG LABEL
Date: 20251108
DEA Schedule: CIV

ACTIVE INGREDIENTS: DIFENOXIN HYDROCHLORIDE 1 mg/1 1; ATROPINE SULFATE 0.025 mg/1 1
INACTIVE INGREDIENTS: CALCIUM STEARATE; STARCH, CORN; CELLULOSE, MICROCRYSTALLINE; ANHYDROUS LACTOSE

Motofen® (difenoxin and atropine sulfate tablets) CIV
Rx Only

DESCRIPTION

Each five-sided dye free MOTOFEN® tablet contains: 1 mg of difenoxin (equivalent to 1.09 mg of difenoxin hydrochloride) and 0.025 mg of atropine sulfate (equivalent to 0.01 mg of atropine).

Difenoxin hydrochloride, 1-(3-cyano-3,3-diphenylpropyl)-4-phenyl-4-piperidinecarboxylic acid monohydrochloride, is an orally administered antidiarrheal agent which is chemically related to the narcotic meperidine.

The structural formula is:

Atropine sulfate is present to discourage deliberate overdose.

Atropine sulfate, an anticholinergic, is benzeneacetic acid, α-(hydroxymethyl)-, 8-methyl-8-azabicyclo[3.2.1]oct-3-yl ester, endo-(±)-, (2:1) (salt), monohydrate and has the following structural formula:

Inactive Ingredients: calcium stearate, cellulose, lactose, corn starch.

CLINICAL PHARMACOLOGY

Animal studies have shown that difenoxin hydrochloride manifests its antidiarrheal effect by slowing intestinal motility. The mechanism of action is by a local effect on the gastrointestinal wall.

Difenoxin is the principal active metabolite of diphenoxylate.

Following oral administration of MOTOFEN®, difenoxin is rapidly and extensively absorbed. Mean peak plasma levels of approximately 160 ng/mL occurred within 40 to 60 minutes in most patients following an oral dose of 2 mg. Plasma levels decline to less than 10% of their peak values within 24 hours and to less than 1% of their peak values within 72 hours. This decline parallels the appearance of difenoxin and its metabolites in the urine. Difenoxin is metabolized to an inactive hydroxylated metabolite. Both the drug and its metabolites are excreted, mainly as conjugates, in urine and feces.

INDICATIONS AND USAGE

MOTOFEN® is indicated as adjunctive therapy in the management of acute nonspecific diarrhea and acute exacerbations of chronic functional diarrhea.

CONTRAINDICATIONS

MOTOFEN® is contraindicated in patients with diarrhea associated with organisms that penetrate the intestinal mucosa (toxigenic E. coli, Salmonella species, Shigella) and pseudomembranous colitis associated with broad spectrum antibiotics. Antiperistaltic agents should not be used in the conditions because they may prolong and/or worsen diarrhea.

MOTOFEN® is contraindicated in children under 2 years of age because of the decreased margin of safety of drugs in this class in younger age groups.

MOTOFEN® is contraindicated in patients with a known hypersensitivity to difenoxin, atropine, or any of the inactive ingredients, and in patients who are jaundiced.

WARNINGS

MOTOFEN® IS NOT AN INNOCUOUS DRUG AND DOSAGE RECOMMENDATIONS SHOULD BE STRICTLY ADHERED TO. MOTOFEN® IS NOT RECOMMENDED FOR CHILDREN UNDER 2 YEARS OF AGE. OVERDOSAGE MAY RESULT IN SEVERE RESPIRATORY DEPRESSION AND COMA, POSSIBLY LEADING TO PERMANENT BRAIN DAMAGE OR DEATH (SEE OVERDOSAGE). THEREFORE, KEEP THIS MEDICATION OUT OF THE REACH OF CHILDREN.

FLUID AND ELECTROLYTE BALANCE – THE USE OF MOTOFEN® DOES NOT PRECLUDE THE ADMINISTRATION OF APPROPRIATE FLUID AND ELECTROLYTE THERAPY. DEHYDRATION, PARTICULARLY IN CHILDREN, MAY FURTHER INFLUENCE THE VARIABILITY OF RESPONSE TO MOTOFEN® AND MAY PREDISPOSE TO DELAYED DIFENOXIN INTOXICATION. DRUG-INDUCED INHIBITION OF PERISTALSIS MAY RESULT IN FLUID RETENTION IN THE COLON, AND THIS MAY FURTHER AGGRAVATE DEHYDRATION AND ELECTROLYTE IMBALANCE.

IF SEVERE DEHYDRATION OR ELECTROLYTE IMBALANCE IS MANIFESTED, MOTOFEN® SHOULD BE WITHHELD UNTIL APPROPRIATE CORRECTIVE THERAPY HAS BEEN INITIATED.

Ulcerative Colitis – In some patients with acute ulcerative colitis, agents which inhibit intestinal motility or delay intestinal transit time have been reported to induce toxic megacolon. Consequently, patients with acute ulcerative colitis should be carefully observed and MOTOFEN® therapy should be discontinued promptly if abdominal distention occurs or if other untoward symptoms develop.

Liver and Kidney Disease – MOTOFEN® should be used with extreme caution in patients with advanced hepatorenal disease and in all patients with abnormal liver function tests since hepatic coma may be precipitated.

Atropine – A subtherapeutic dose of atropine has been added to difenoxin hydrochloride to discourage deliberate overdosage. Usage of MOTOFEN® in recommended doses is not likely to cause prominent anticholinergic side effects, but MOTOFEN® should be avoided in patients in whom anticholinergic drugs are contraindicated. The warnings and precautions for use of anticholinergic agents should be observed. In children, signs of atropinism may occur even with recommended doses of MOTOFEN®, particularly in patients with Down’s Syndrome.

PRECAUTIONS

CAUTION PATIENTS TO ADHERE STRICTLY TO RECOMMENDED DOSAGE SCHEDULES. THE MEDICATION SHOULD BE KEPT OUT OF REACH OF CHILDREN SINCE ACCIDENTAL OVERDOSAGE MAY RESULT IN SEVERE, EVEN FATAL, RESPIRATORY DEPRESSION.

MOTOFEN® may produce drowsiness or dizziness. The patient should be cautioned regarding activities requiring mental alertness, such as driving or operating dangerous machinery.

Drug Interactions

Since the chemical structure of difenoxin hydrochloride is similar to meperidine hydrochloride, the concurrent use of MOTOFEN® with monoamine oxidase inhibitors may, in theory, precipitate a hypertensive crisis.

MOTOFEN® may potentiate the action of barbiturates, tranquilizers, narcotics, and alcohol. When these medications are used concomitantly with MOTOFEN®, the patient should be closely monitored.

Diphenoxylate hydrochloride, from which the principal active metabolite difenoxin is derived, was found to inhibit the hepatic microsomal enzyme system at a dose of 2 mg/kg/day in studies conducted with male rats. Therefore, difenoxin has the potential to prolong the biological half-lives of drugs for which the rate of elimination is dependent on the microsomal drug metabolizing enzyme system.

Carcinogenesis, Mutagensis, Impairment of Fertility

No evidence of carcinogenesis was found in a long-term study of difenoxin hydrochloride/atropine in the rat. In this 104 week study, rats received dietary doses of 0, 1.25, 2.5, or 5 mg/kg/day difenoxin/atropine (20:1 ratio).

No experiments have been conducted to determine the mutagenic potential of MOTOFEN®. MOTOFEN® did not

significantly impair fertility in rats.

Pregnancy/Teratogenic Effects

Pregnancy Category C. Reproduction studies in rats and rabbits with doses at 31 and 61 times the human therapeutic dose respectively, on a mg/kg basis, demonstrated no evidence of teratogenesis due to MOTOFEN®.

Pregnant rats receiving oral doses of difenoxin hydrochloride/atropine 20 times the maximum human dose had an increase in delivery time as well as a significant increase in the percent of stillbirths.

Neonatal survival in rats was also reduced with most deaths occurring within four days of delivery.

There are no well controlled studies in pregnant women. MOTOFEN® should be used during pregnancy only if the potential benefit justifies the potential risk of the fetus.

Nursing Mothers

Because of the potential for serious adverse reactions in nursing infants from MOTOFEN®, a decision should be made whether to discontinue nursing or to discontinue the drug, taking into account the importance of the drug to the mother.

Pediatric Use

SAFETY AND EFFECTIVENESS IN CHILDREN BELOW THE AGE OF 12 HAVE NOT BEEN ESTABLISHED. MOTOFEN® IS CONTRAINDICATED IN CHILDREN UNDER 2 YEARS OF AGE. See OVERDOSAGE section for information on hazards from accidental poisoning in children.

ADVERSE REACTIONS

In view of the small amount of atropine present (0.025 mg/tablet), such effects such as dryness of the skin and mucous membranes, flushing, hyperthermia, tachycardia and urinary retention are very unlikely to occur, except perhaps in children. Many of the adverse effects reported during clinical investigation of MOTOFEN® are difficult to distinguish from symptoms associated with the diarrheal syndrome. However, the following events were reported at the stated frequencies:

Gastrointestinal: Nausea, 1 in 15 patients; vomiting, 1 in 30 patients; dry mouth, 1 in 30 patients; epigastric distress, 1 in 100 patients; and constipation, 1 in 300 patients.

Central Nervous System: Dizziness and light-headedness, 1 in 20 patients; drowsiness, 1 in 25 patients; and headache, 1 in 40 patients; tiredness, nervousness, insomnia and confusion ranged from 1 in 200 to 1 in 600 patients.

Other less frequent reactions: Burning eyes and blurred vision occurred in a few cases.

The following adverse reactions have been reported in patients receiving chemically-related drugs: numbness of extremities, euphoria, depression, sedation, anaphylaxis, angioneurotic edema, urticaria, swelling of the gums, pruritus, toxic megacolon, paralytic ileus, pancreatitis, and anorexia.

THIS MEDICATION SHOULD BE KEPT IN A CHILD-RESISTANT CONTAINER AND OUT OF THE REACH OF CHILDREN SINCE AN OVERDOSAGE MAY RESULT IN SEVERE RESPIRATORY DEPRESSION AND COMA, POSSIBLY LEADING TO PERMANENT BRAIN DAMAGE OR DEATH.

DRUG ABUSE AND DEPENDENCE

MOTOFEN® tablets are a Schedule IV controlled substance.

Addiction to (dependence on) difenoxin hydrochloride is theoretically possible at high dosage. Therefore, the recommended dosage should not be exceeded. Because of the structural and pharmacological similarities of difenoxin hydrochloride to drugs with a definite addiction potential, MOTOFEN® should be administered with considerable caution to patients who are receiving addicting drugs, to individuals known to be addiction prone, or to those in whom histories suggest may increase dosage on their own initiative.

Diagnosis and Treatment

In the event of overdosage (initial signs may include dryness of the skin and mucous membranes, flushing, hyperthermia and tachycardia followed by lethargy or coma, hypotonic reflexes, nystagmus, pinpoint pupils and respiratory depression) gastric lavage, establishment of a patent airway and possibly mechanically assisted respiration are advised.

The narcotic antagonist naloxone may be used in the treatment of respiratory depression caused by narcotic analgesics of pharmacologically related compounds such as MOTOFEN® tablets. When naloxone is administered intravenously, the onset of action is generally apparent within two minutes. Naloxone may be administered subcutaneously or intramuscularly providing a slightly less rapid onset of action but a more prolonged effect.

To counteract respiratory depression caused by MOTOFEN® overdosage, the following dosage schedule for naloxone should be followed:

Adult Dosage: The usual initial adult dose of naloxone is 0.4 mg (one mL) administered intravenously. If respiratory

function does not adequately improve after the initial dose, the same IV dose may be repeated at two-to-three minute

intervals.

Children: The usual adult dose of naloxone for children is 0.01 mg/kg of body weight administered intravenously and
repeated at two-to-three minute intervals if necessary.

Since the duration of action of difenoxin hydrochloride is longer than that of naloxone, improvement of respiration following administration may be followed by recurrent respiratory depression. Consequently, continuous observation is necessary until the effect of difenoxin hydrochloride on respiration (which effect may persist for many hours) has passed. Supplemental
intramuscular doses of naloxone may be utilized to produce a longer lasting effect. TREAT ALL POSSIBLE MOTOFEN® OVERDOSAGES AS SERIOUS AND MAINTAIN MEDICAL OBSERVATION FOR AT LEAST 48 HOURS, PREFERABLY UNDER CONTINUOUS HOSPITAL CARE.

Although signs of overdosage and respiratory depression may not be evident soon after ingestion of difenoxin
hydrochloride, respiratory depression may occur from 12 to 30 hours later.

DOSAGE AND ADMINISTRATION

The recommended starting dose of MOTOFEN® tablets in adults is 2 tablets then 1 tablet after each loose stool or 1 tablet every 3 to 4 hours as needed, but the total dosage during any 24-hour treatment period should not exceed 8 tablets. In the treatment of diarrhea, if clinical improvement is not observed in 48 hours, continued administration of this type of medication is not recommended. For acute diarrheas and acute exacerbations of functional diarrhea, treatment beyond 48 hours is usually not necessary.

Studies in children below the age of 12 have been inadequate to evaluate the safety and effectiveness of MOTOFEN® in this age group. MOTOFEN® is contraindicated in children under 2 years of age.

HOW SUPPLIED

MOTOFEN® is available as a white, dye-free, five-sided, scored tablet with “0200” on the scored side and "M" on the other side. Each tablet contains 1 mg difenoxin and 0.025 mg atropine sulfate. Supplied in bottles of 100 tablets (NDC 54766-200-10). Store at 20°-25°C (68°-77°F) [See USP Controlled Room Temperature].

Distributed by:

Sebela Pharmaceuticals Inc.

645 Hembree Parkway, Suite I

Roswell, GA 30076

www.sebelapharma.com

Motofen is a registered trademark of Sebela International Limited

PI 20010 0217

Rev. Mar. 2017